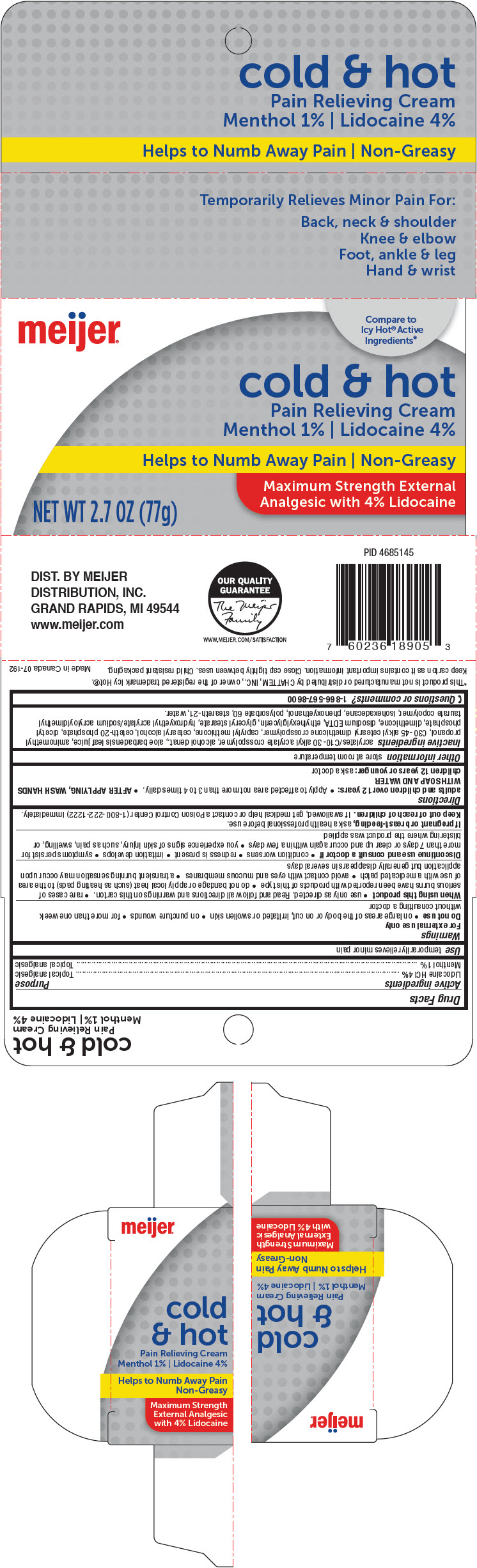 DRUG LABEL: Meijer Cold and Hot Pain Relieving
NDC: 41250-355 | Form: CREAM
Manufacturer: Meijer Distribution, Inc
Category: otc | Type: HUMAN OTC DRUG LABEL
Date: 20241106

ACTIVE INGREDIENTS: Lidocaine Hydrochloride 40 mg/1 g; MENTHOL, UNSPECIFIED FORM 10 mg/1 g
INACTIVE INGREDIENTS: CARBOMER INTERPOLYMER TYPE A (ALLYL SUCROSE CROSSLINKED); ALCOHOL; ALOE VERA LEAF; AMINOMETHYLPROPANOL; CAPRYLYL TRISILOXANE; CETOSTEARYL ALCOHOL; Ceteth-20 Phosphate; DIHEXADECYL PHOSPHATE; DIMETHICONE; EDETATE DISODIUM; Ethylhexylglycerin; GLYCERYL MONOSTEARATE; HYDROXYETHYL ACRYLATE/SODIUM ACRYLOYLDIMETHYL TAURATE COPOLYMER (100000 MPA.S AT 1.5%); Isohexadecane; Phenoxyethanol; Polysorbate 60; Steareth-21; Water

Meijer® Cold & Hot Pain Relieving Cream
Topical Analgesic

Drug Facts

ACTIVE INGREDIENT

Active ingredients | Purpose
Lidocaine HCl 4% | Topical analgesic
Menthol 1% | Topical analgesic

Use

temporarily relieves minor pain

Warnings

For external use only

Do not use

- on large areas of the body or on cut, irritated or swollen skin
- on puncture wounds
- for more than one week without consulting a doctor

When using this product

- use only as directed. Read and follow all directions and warnings on this carton.
- rare cases of serious burns have been reported with products of this type
- do not bandage or apply local heat (such as heating pads) to the area of use with a medicated patch
- avoid contact with eyes and mucous membranes
- a transient burning sensation may occur upon application but generally disappears in several days

Discontinue use and consult a doctor if

- condition worsens
- redness is present
- irritation develops
- symptoms persist for more than 7 days or clear up and occur again within a few days
- you experience signs of skin injury, such as pain, swelling, or blistering where the product was applied

PREGNANCY OR BREAST FEEDING

If pregnant or breast-feeding, ask a health professional before use.

Keep out of reach of children. If swallowed, get medical help or contact a Poison Control Center (1-800-222-1222) immediately.

Directions

adults and children over 12 years:

- Apply to affected area not more than 3 to 4 times daily.
- AFTER APPLYING, WASH HANDS WITH SOAP AND WATER

children 12 years or younger: ask a doctor

Other information

store at room temperature

Inactive ingredients

acrylates/C10-30 alkyl acrylate crosspolymer, alcohol denat., aloe barbadensis leaf juice, aminomethyl propanol, C30-45 alkyl cetearyl dimethicone crosspolymer, caprylyl methicone, cetearyl alcohol, ceteth-20 phosphate, dicetyl phosphate, dimethicone, disodium EDTA, ethylhexylglycerin, glyceryl stearate, hydroxyethyl acrylate/sodium acryloyldimethyl taurate copolymer, isohexadecane, phenoxyethanol, polysorbate 60, steareth-21, water.

Questions or comments?

1-866-567-8600

DIST. BY MEIJER
DISTRIBUTION, INC.
GRAND RAPIDS, MI 49544

PRINCIPAL DISPLAY PANEL - 77 g Bottle Carton

meijer®

Compare to
Icy Hot® Active
Ingredients*

cold & hot
Pain Relieving Cream
Menthol 1% | Lidocaine 4%

Helps to Numb Away Pain | Non-Greasy

Maximum Strength External
Analgesic with 4% Lidocaine

NET WT 2.7 OZ (77g)